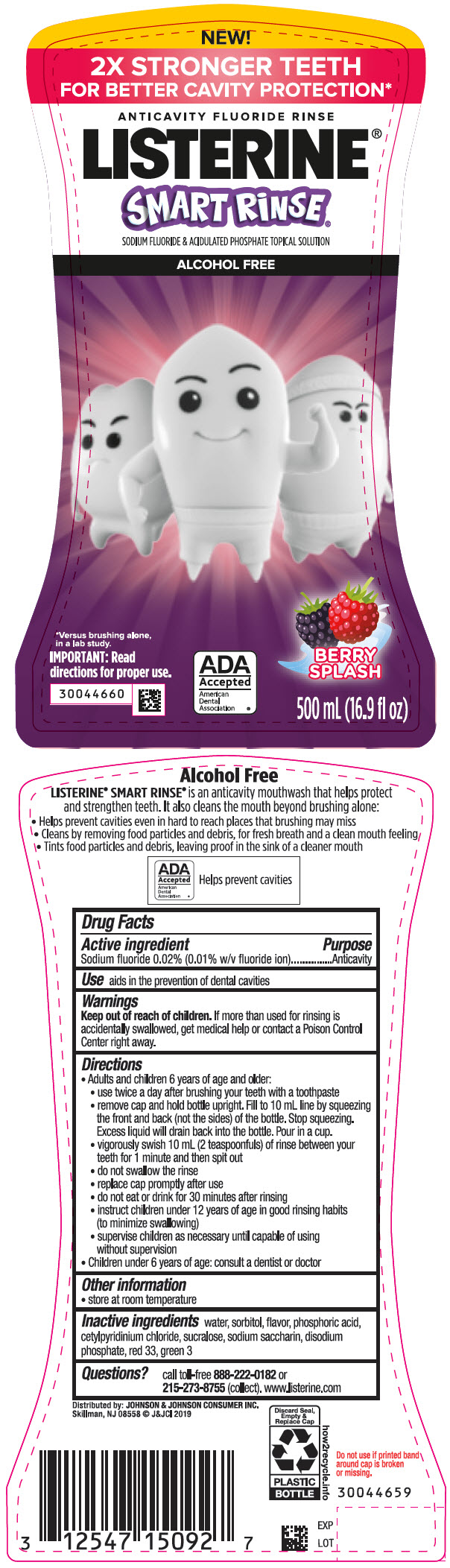 DRUG LABEL: Listerine Smart Rinse Berry Splash
NDC: 69968-0606 | Form: MOUTHWASH
Manufacturer: Kenvue Brands LLC
Category: otc | Type: HUMAN OTC DRUG LABEL
Date: 20241111

ACTIVE INGREDIENTS: SODIUM FLUORIDE 0.1 mg/1 mL
INACTIVE INGREDIENTS: WATER; SORBITOL; PHOSPHORIC ACID; CETYLPYRIDINIUM CHLORIDE; SUCRALOSE; SACCHARIN SODIUM; SODIUM PHOSPHATE, DIBASIC, ANHYDROUS; D&C RED NO. 33; FD&C GREEN NO. 3

LISTERINE® SMART RiNSE® BERRY SPLASH

Drug Facts

Active ingredient

Sodium fluoride 0.02% (0.01% w/v fluoride ion)

Purpose

Anticavity

Use

aids in prevention of dental cavities

Warnings

Keep out of reach of children. If more than used for rinsing is accidentally swallowed, get medical help or contact a Poison Control Center right away.

Directions

- Adults and children 6 years of age and older:
- use twice a day after brushing your teeth with a toothpaste
- remove cap and hold bottle upright. Fill to 10 mL line by squeezing the front and back (not the sides) of the bottle. Stop squeezing. Excess liquid will drain back into the bottle. Pour in the cup.
- vigorously swish 10 mL (2 teaspoonfuls) of rinse between your teeth for 1 minute and then spit out
- do not swallow the rinse
- replace cap promptly after use
- do not eat or drink for 30 minutes after rinsing
- instruct children under 12 years of age in good rinsing habits (to minimize swallowing)
- supervise children as necessary until capable of using without supervision
- Children under 6 years of age: consult a dentist or doctor

Other information

- store at room temperature

Inactive ingredients

water, sorbitol, flavor, phosphoric acid, cetylpyridinium chloride, sucralose, sodium saccharin, disodium phosphate, red 33, green 3

Questions?

call toll-free 888-222-0182 or 215-273-8755 (collect). www.listerine.com

Distributed by: JOHNSON & JOHNSON CONSUMER INC.
Skillman, NJ 08558

PRINCIPAL DISPLAY PANEL - 500 mL Bottle Label

NEW!
2X STRONGER TEETH
FOR BETTER CAVITY PROTECTION*
ANTICAVITY FLUORIDE RINSE
LISTERINE®
SMART RiNSE®
SODIUM FLUORIDE & ACIDULATED PHOSPHATE TOPICAL SOLUTION
ALCOHOL FREE

*Versus brushing alone,
In a lab study.
IMPORTANT: Read
directions for proper use.

ADA
Accepted
American
Dental
Association ®

BERRY
SLASH
500 mL (16.9 fl oz)